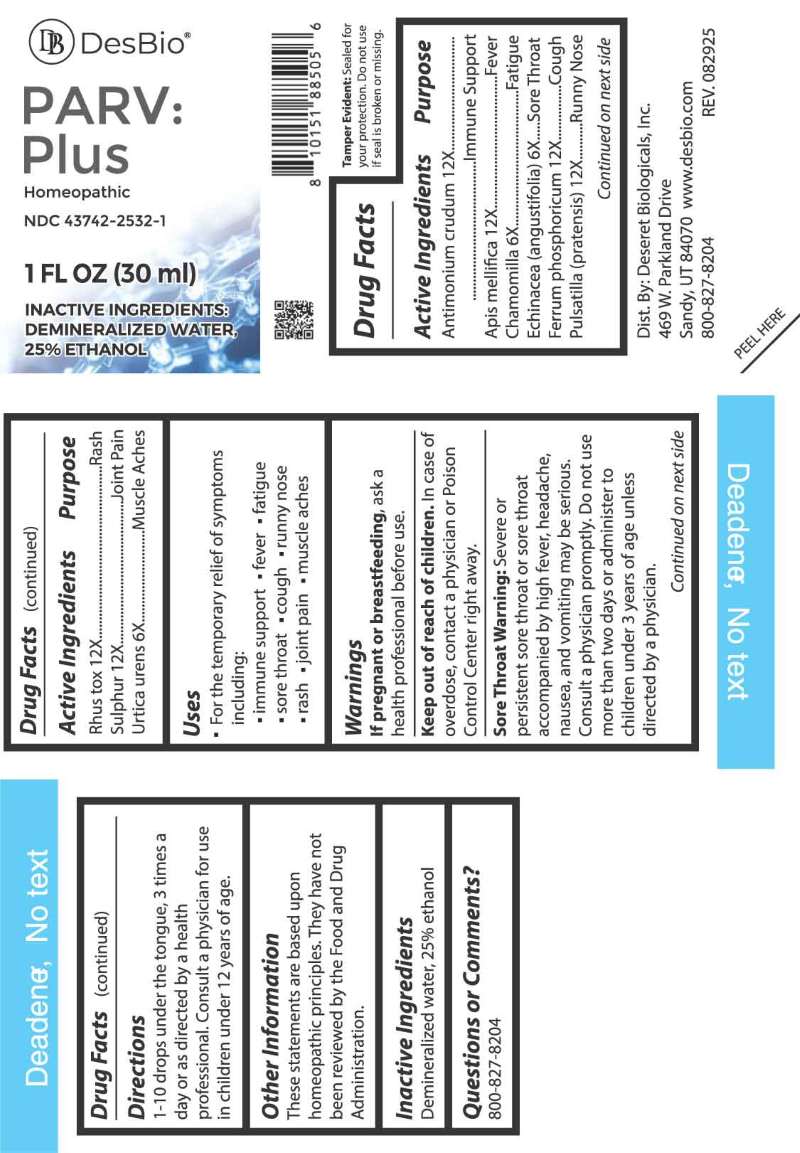 DRUG LABEL: PARV Plus
NDC: 43742-2532 | Form: LIQUID
Manufacturer: Deseret Biologicals, Inc.
Category: homeopathic | Type: HUMAN OTC DRUG LABEL
Date: 20260102

ACTIVE INGREDIENTS: ANTIMONY TRISULFIDE 12 [hp_X]/1 mL; APIS MELLIFERA 12 [hp_X]/1 mL; MATRICARIA CHAMOMILLA WHOLE 6 [hp_X]/1 mL; ECHINACEA ANGUSTIFOLIA WHOLE 6 [hp_X]/1 mL; FERROSOFERRIC PHOSPHATE 12 [hp_X]/1 mL; PULSATILLA PRATENSIS WHOLE 12 [hp_X]/1 mL; TOXICODENDRON PUBESCENS LEAF 12 [hp_X]/1 mL; SULFUR 12 [hp_X]/1 mL; URTICA URENS WHOLE 6 [hp_X]/1 mL
INACTIVE INGREDIENTS: WATER; ALCOHOL

DRUG FACTS:

ACTIVE INGREDIENTS:

Antimonium Crudum 12X, Apis Mellifica 12X, Chamomilla 6X, Echinacea (Angustifolia) 6X, Ferrum Phosphoricum 12X, Pulsatilla (Pratensis) 12X, Rhus Tox 12X, Sulphur 12X, Urtica Urens 6X.

PURPOSE:

Antimonium Crudum – Immune Support, Apis Mellifica - Fever, Chamomilla - Fatigue, Echinacea (Angustifolia) – Sore Throat, Ferrum Phosphoricum - Cough, Pulsatilla (Pratensis) – Runny Nose, Rhus Tox - Rash, Sulphur – Joint Pain, Urtica Urens – Muscle Aches

USES:

• For the temporary relief of symptoms including:

• immune support • fever • fatigue • sore throat • cough

• runny nose • rash • joint pain • muscle aches

These statements are based upon homeopathic principles. They have not been reviewed by the Food and Drug Administration.

WARNINGS:

If pregnant or breastfeeding, ask a health professional before use.

Keep out of reach of children. In case of overdose, contact a physician or Poison Control Center right away.

Sore Throat Warning: Severe or persistent sore throat or sore throat accompanied by high fever, headache, nausea, and vomiting may be serious. Consult a physician promptly. Do not use more than two days or administer to children under 3 years of age unless directed by a physician.

Tamper Evident: Sealed for your protection. Do not use if seal is broken or missing.

KEEP OUT OF REACH OF CHILDREN:

In case of overdose, contact a physician or Poison Control Center right away.

DIRECTIONS:

1-10 drops under the tongue, 3 times a day or as directed by a health professional. Consult a physician for use in children under 12 years of age.

INACTIVE INGREDIENTS:

Demineralized water, 25% ethanol

QUESTIONS:

Dist. By: Deseret Biologicals, Inc.

469 W. Parkland Drive

Sandy, UT 84070

www.desbio.com

800-827-8204

PACKAGE DISPLAY LABEL:

DesBio

PARV:Plus

Homeopathic

NDC 43742-2532-1

1 FL OZ (30 ml)